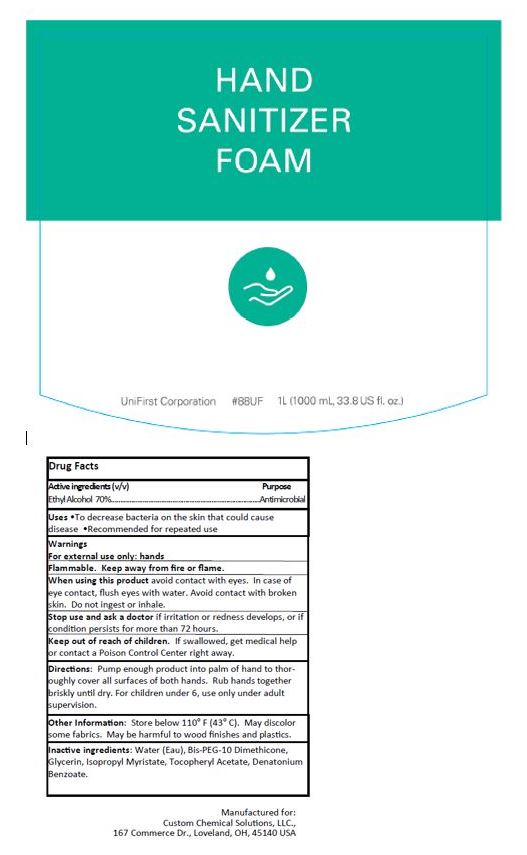 DRUG LABEL: Hand Sanitizer Foam
NDC: 77955-002 | Form: SOLUTION
Manufacturer: Custom Chemical Solutions
Category: otc | Type: HUMAN OTC DRUG LABEL
Date: 20240122

ACTIVE INGREDIENTS: ALCOHOL 70 mL/100 mL
INACTIVE INGREDIENTS: .ALPHA.-TOCOPHEROL ACETATE; WATER; ISOPROPYL MYRISTATE; DENATONIUM BENZOATE; GLYCERIN; BIS-PEG-10 DIMETHICONE/DIMER DILINOLEATE COPOLYMER

77955-002

Active ingredients (v/v)

Ethyl Alcohol 70%

Purpose

Antimicrobial

Uses

- To decrease bacteria on the skin that could cause disease
- Recommended for repeated use

Warnings

For external use only: hands

Flammable. Keep away from fire or flame.

When using this productavoid contact with eyes.

In case of eye contact, flush eyes with water.

Avoid contact with broken skin.

Do not ingest or inhale.

Stop use and ask a doctorif irritation or redness develops, or if condition persists for more than 72 hours.

Keep out of reach of children.

If swallowed, get medical help or contact a Poison Control Center right away.

Directions:

Pump enough product into palm of hand to thoroughly cover all surfaces of both hands.

Rub hands together briskly until dry.

For children under 6, use only under adult supervision.

Other information:

Store below 110 F (43 C).

May discolor some fabrics.

May be harmful to wood finishes and plastics.

Inactive ingredients:

Water (Eau), Bis-PEG-10 Dimethicone, Glycerin, Isopropyl Myristate, Tocopheryl Acetate, Denatonium Benzoate

PACKAGE LABEL

HAND

SANITIZER

FOAM

UniFirst Corporation 88UF 1L (1000 mL, 33.8 US fl. oz.)